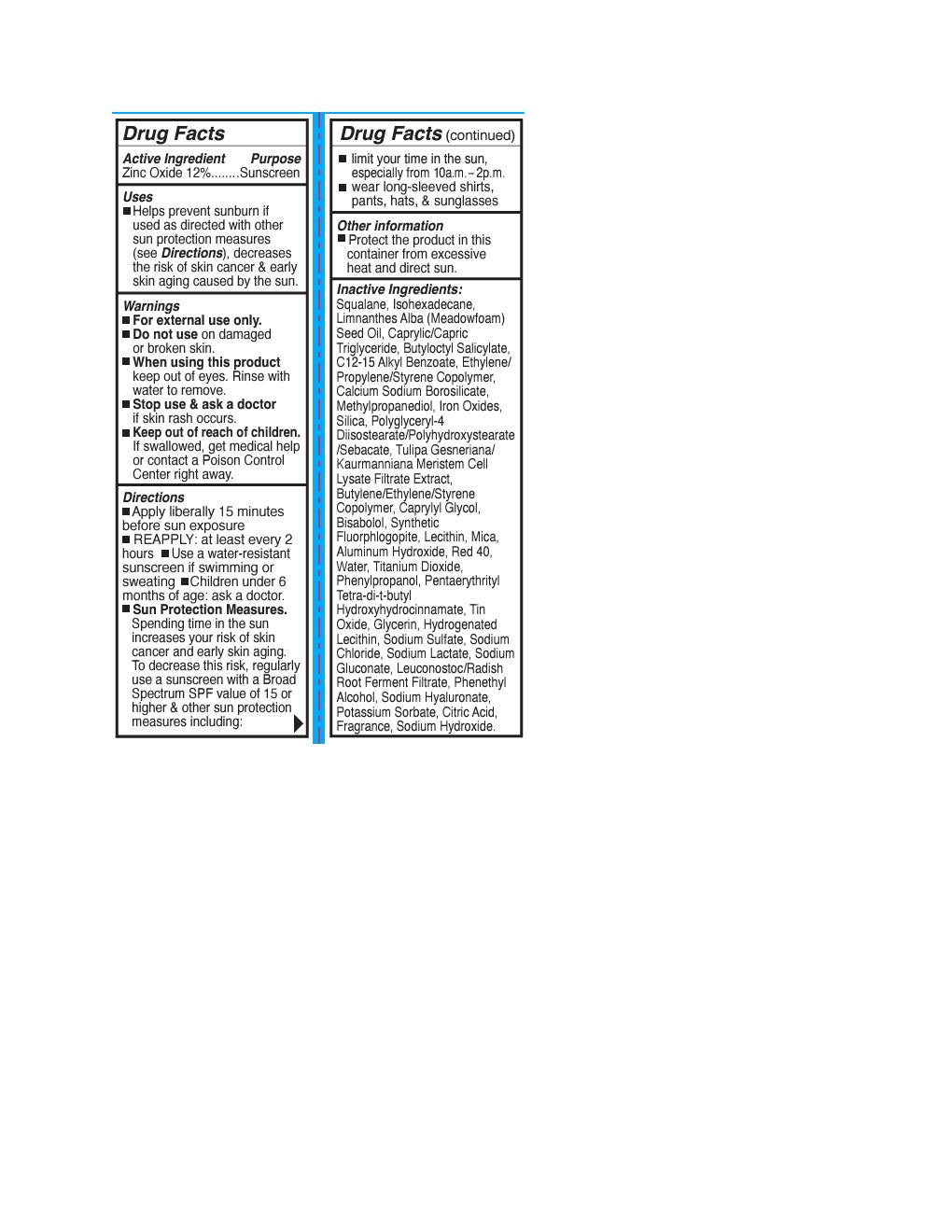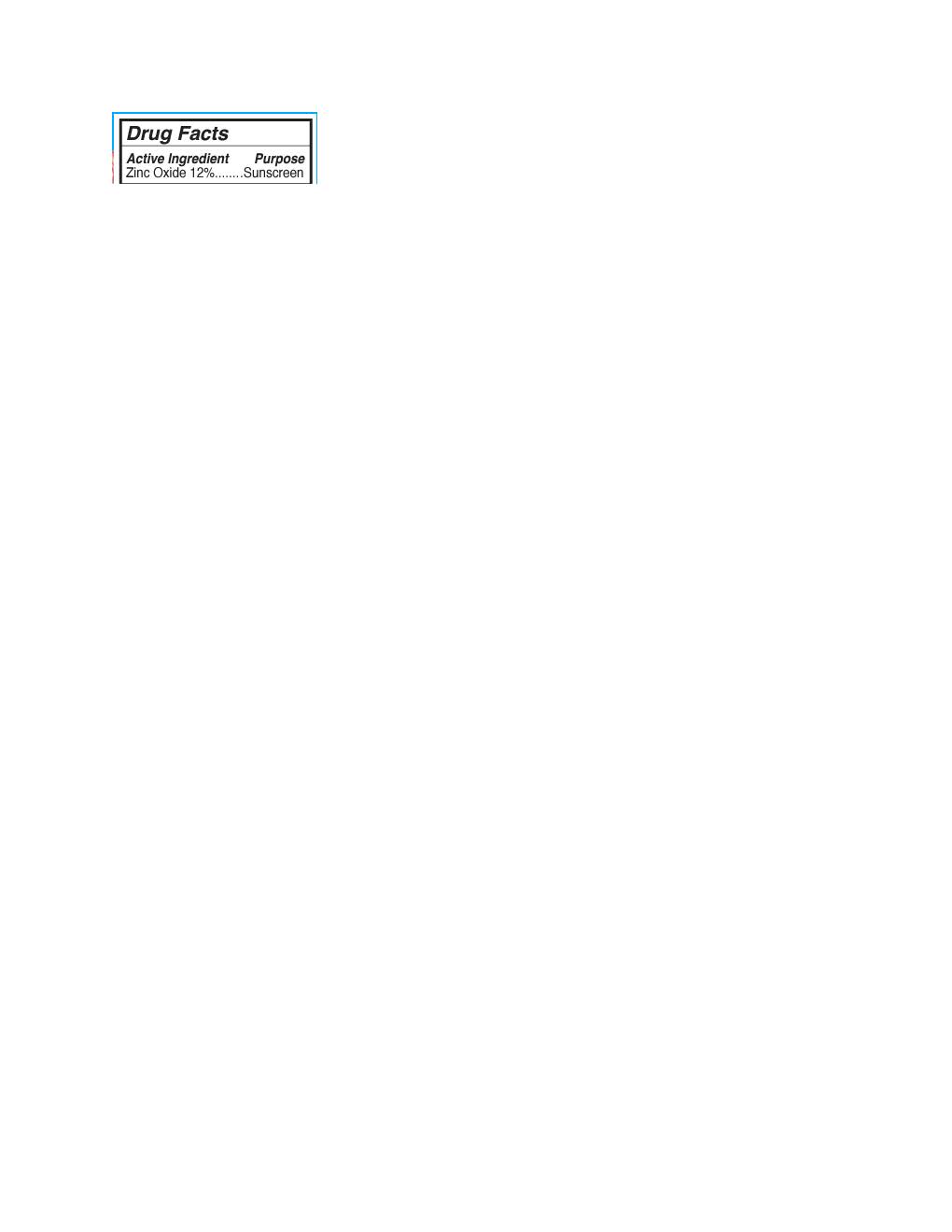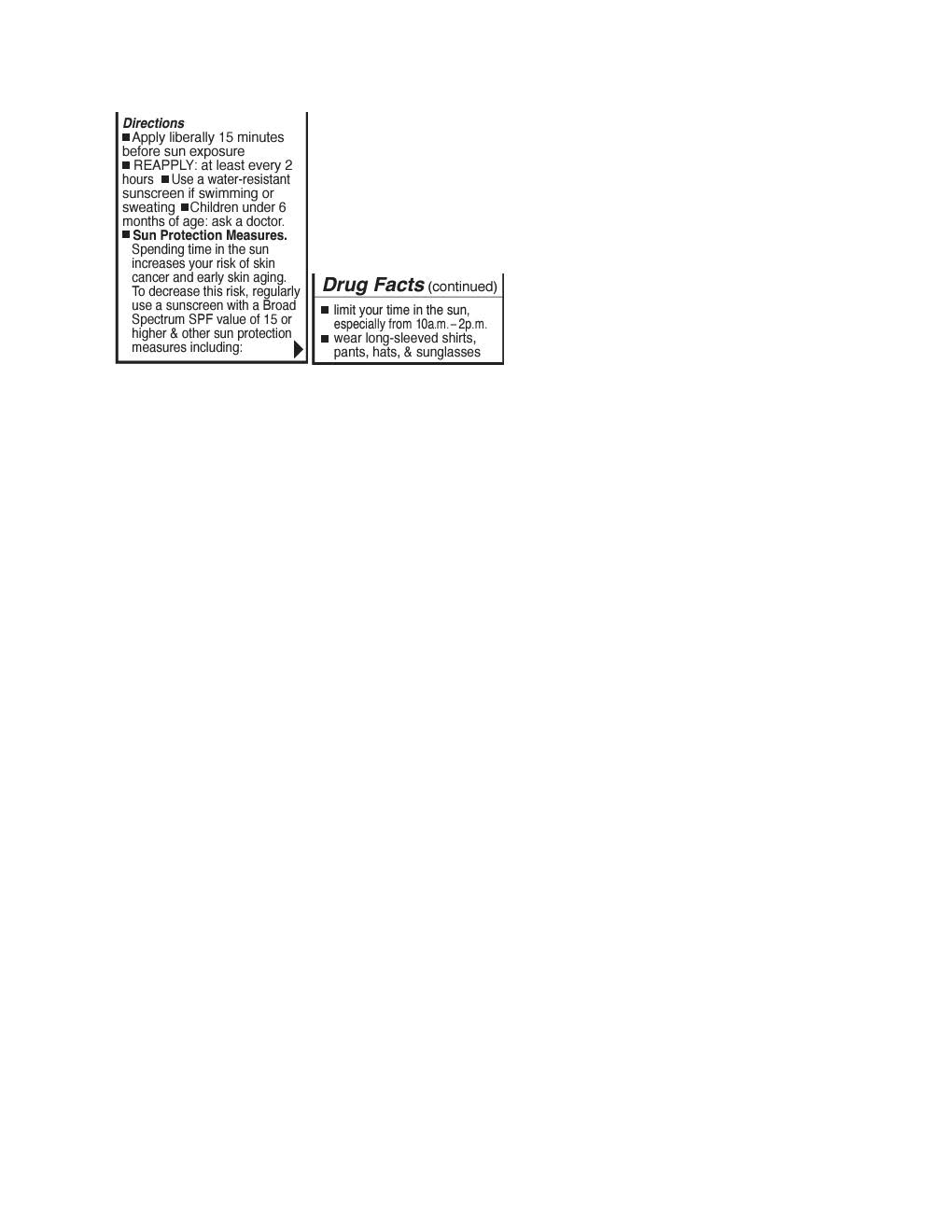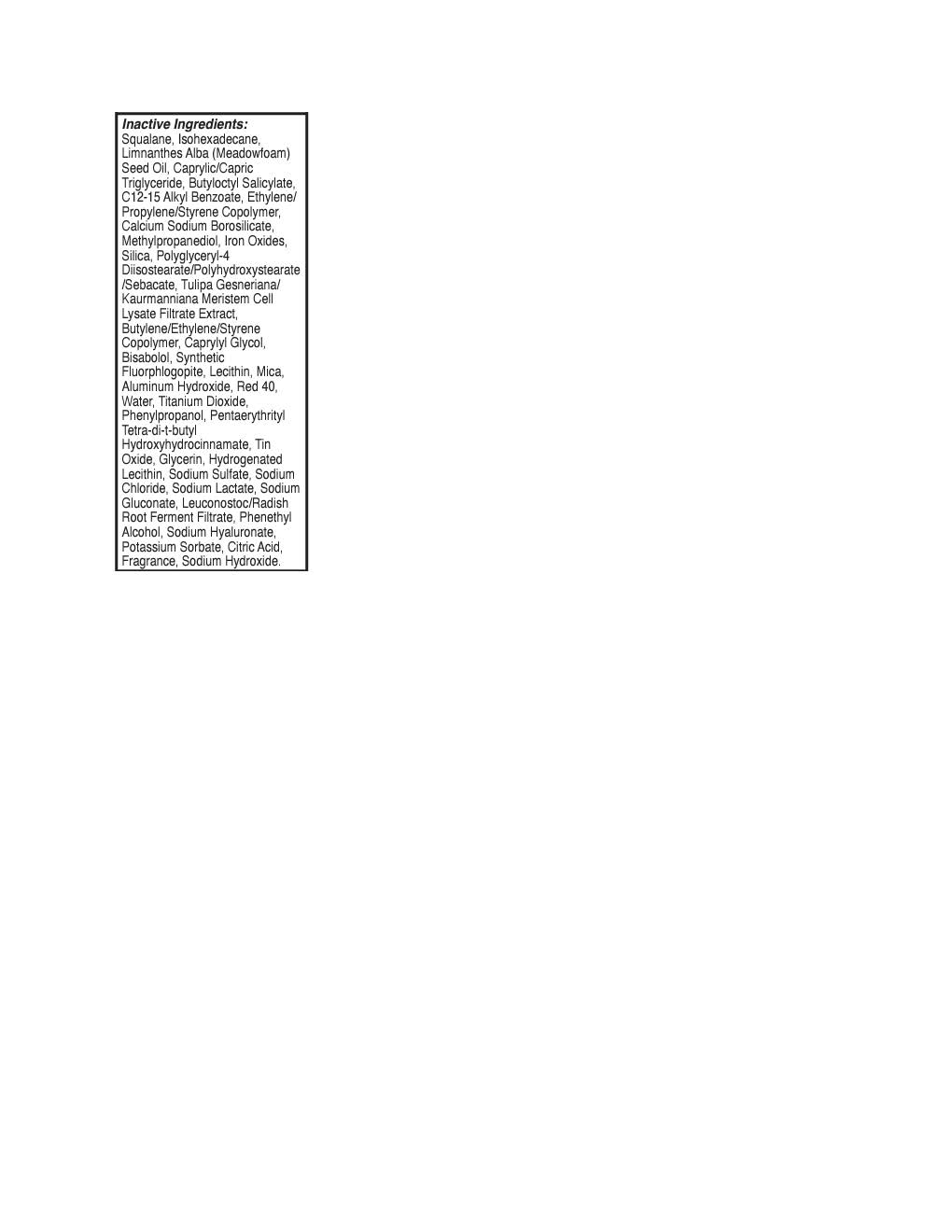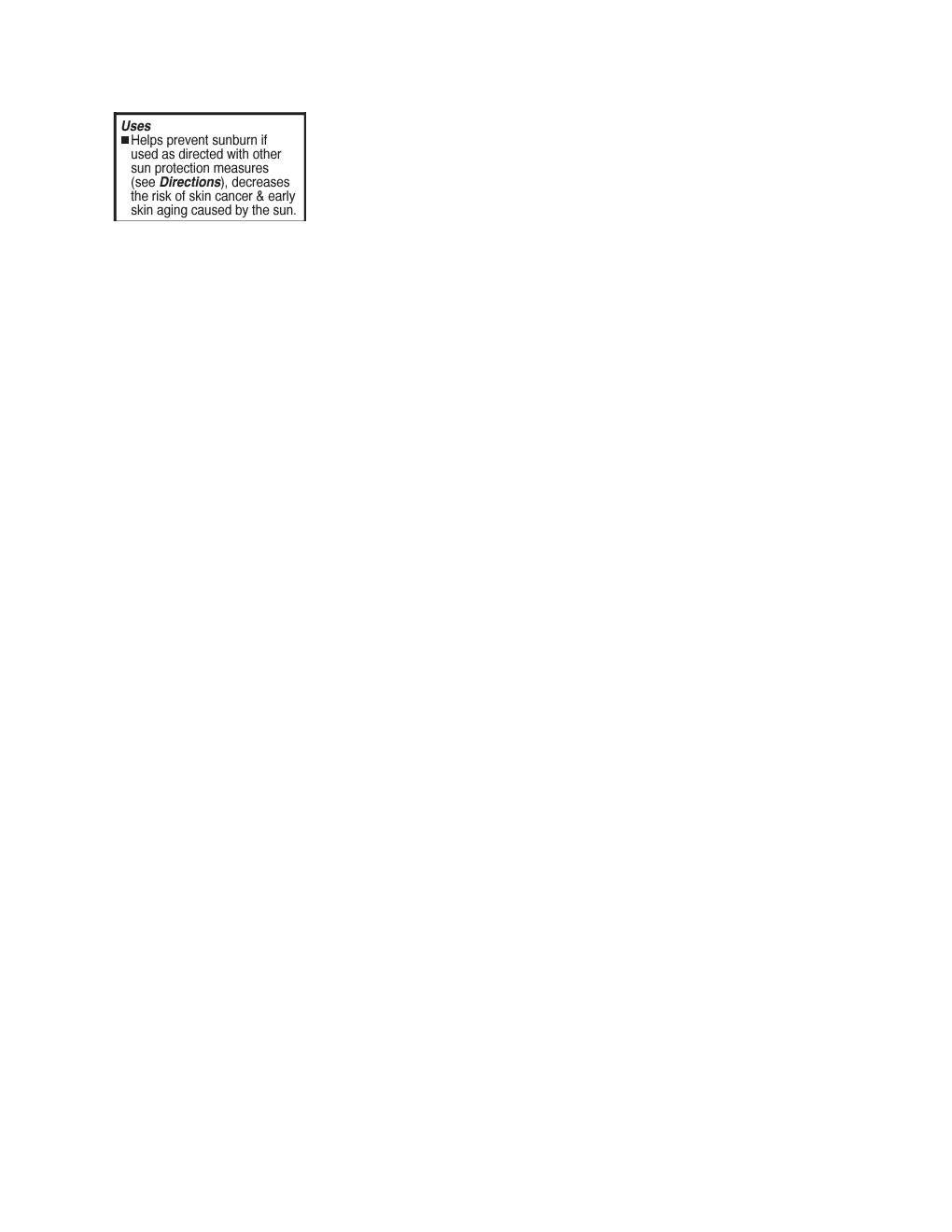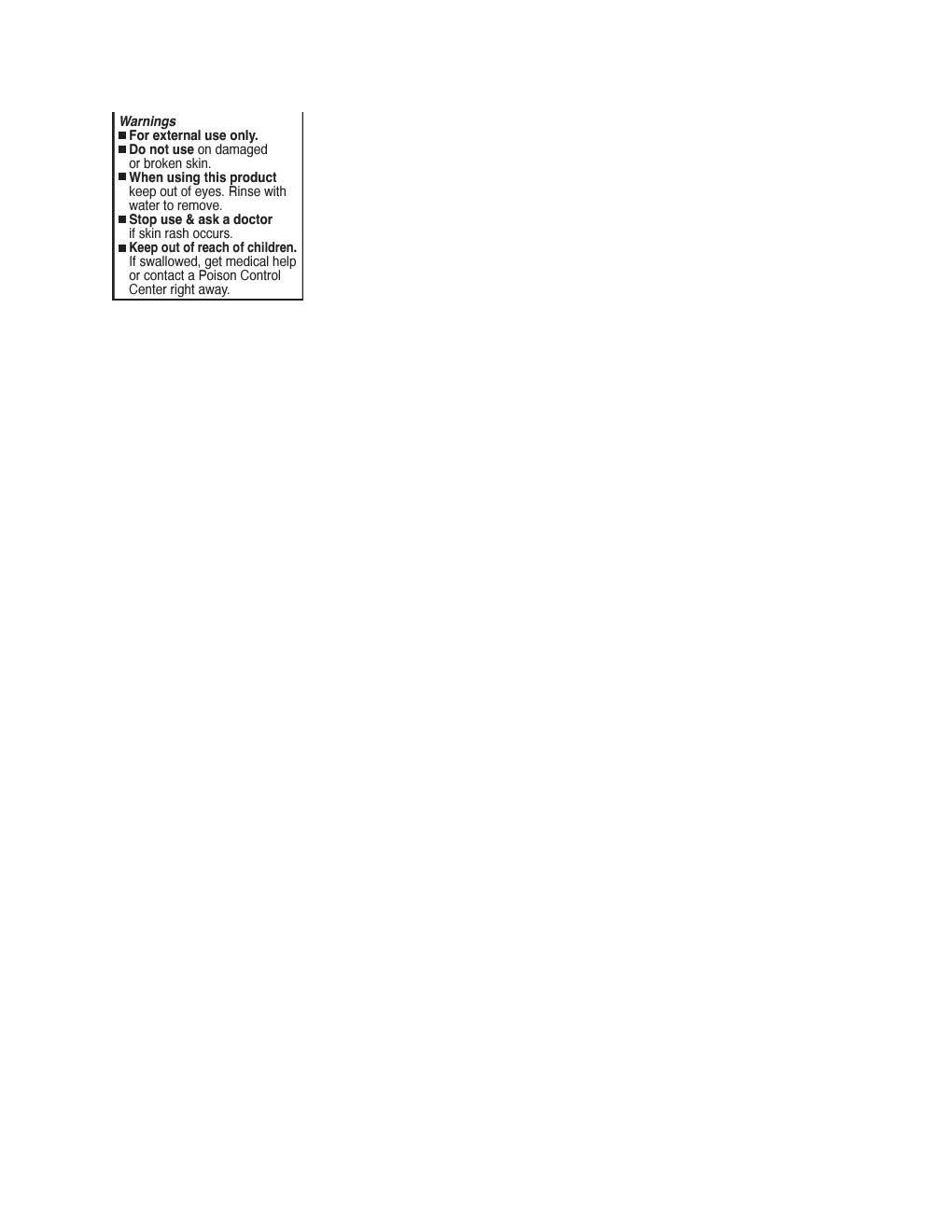 DRUG LABEL: Bloomeffects Tulipscreen Hydrating Lip Oil
NDC: 82548-2341 | Form: LOTION
Manufacturer: Bloomeffects
Category: otc | Type: HUMAN OTC DRUG LABEL
Date: 20251015

ACTIVE INGREDIENTS: ZINC OXIDE 132 mg/1 mL
INACTIVE INGREDIENTS: CALCIUM SODIUM BOROSILICATE; LEUCONOSTOC/RADISH ROOT FERMENT FILTRATE; ISOHEXADECANE; SQUALANE; BUTYLOCTYL SALICYLATE; PROPANEDIOL; PHENYLPROPANOL; TITANIUM DIOXIDE; FERRIC OXIDE RED; LIMNANTHES ALBA WHOLE; .ALPHA.-BISABOLOL, (+)-; CAPRYLYL GLYCOL; MICA; FERRIC OXIDE YELLOW; SILICON DIOXIDE; SODIUM LACTATE; SODIUM GLUCONATE; POTASSIUM SORBATE; SODIUM SULFATE; ALKYL (C12-15) BENZOATE; METHYLPROPANEDIOL; SODIUM HYDROXIDE; LECITHIN, SOYBEAN; WATER; GLYCERIN; POLYGLYCERYL-4 DIISOSTEARATE/POLYHYDROXYSTEARATE/SEBACATE; ALUMINUM HYDROXIDE; SODIUM CHLORIDE

Bloomeffects Tulipscreen Hydrating Lip Oil